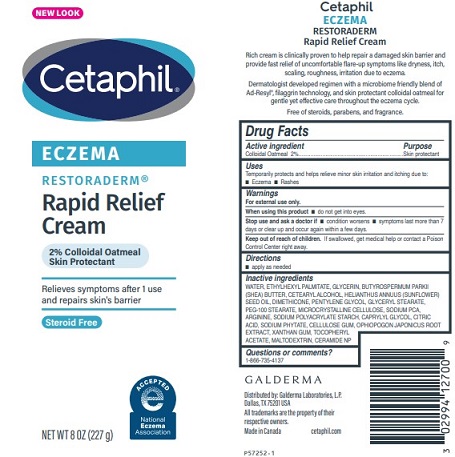 DRUG LABEL: Cetaphil Eczema Rapid Relief Cream
NDC: 0299-4144 | Form: CREAM
Manufacturer: Galderma Laboratories, L.P.
Category: otc | Type: HUMAN OTC DRUG LABEL
Date: 20240502

ACTIVE INGREDIENTS: Oatmeal 2 g/100 g
INACTIVE INGREDIENTS: Water; Ethylhexyl Palmitate; Glycerin; Sheanut Oil; Cetostearyl Alcohol; Sunflower Oil; Dimethicone; Pentylene Glycol; Glyceryl Monostearate; Peg-100 Stearate; Microcrystalline Cellulose; Sodium Pyrrolidone Carboxylate; Arginine; Caprylyl Glycol; Citric Acid Monohydrate; Phytate Sodium; Carboxymethylcellulose Sodium, Unspecified; Ophiopogon Japonicus Root; Xanthan Gum; .Alpha.-Tocopherol Acetate; Maltodextrin; Ceramide Np

Drug Facts

Active ingredients......Purpose

Colloidal Oatmeal 2%......Skin Protectant

Uses

Temporarily protects and helps relieve minor skin irritation and itching due to:
●Eczema ●Rashes

Warnings

For external use only.

When using this product ● do not get into eyes.

Stop use and ask a doctor if ● condition worsens ● symptoms last more than 7 days or clear up and occur again within a few days.

Keep out of reach of children. If swallowed, get medical help or contact a Poison Control Center right away.

Directions

● apply as needed

Inactive Ingredients

WATER, ETHYLHEXYL PALMITATE, GLYCERIN, BUTYROSPERMUM PARKII (SHEA) BUTTER, CETEARYL ALCOHOL, HELIANTHUS ANNUUS (SUNFLOWER) SEED OIL, DIMETHICONE, PENTYLENE GLYCOL, GLYCERYL STEARATE, PEG-100 STEARATE, MICROCRYSTALLINE CELLULOSE, SODIUM PCA, ARGININE, SODIUM POLYACRYLATE STARCH, CAPRYLYL GLYCOL, CITRIC ACID, SODIUM PHYTATE, CELLULOSE GUM, OPHIOPOGON JAPONICUS ROOT EXTRACT, XANTHAN GUM, TOCOPHERYL ACETATE, MALTODEXTRIN, CERAMIDE NP

Questions or comments?

1-866-735-4137

Distributed by:
Galderma Laboratories, L.P.
Dallas, TX 75201

All trademarks are the property of their respective owners

Made in Canada

cetaphil.com

PRINCIPLE DISPLAY PANEL - 8 OZ tube

NEW LOOK
Cetaphil®

ECZEMA

RESTORADERM®

Rapid Relief
Cream

2% Colloidal Oatmeal
Skin Protectant

Relieves symptoms after 1 use
and repairs skin's barrier

Steroid free

National Eczema Association logo

NET WT 8 OZ (227 g)
P57252-1